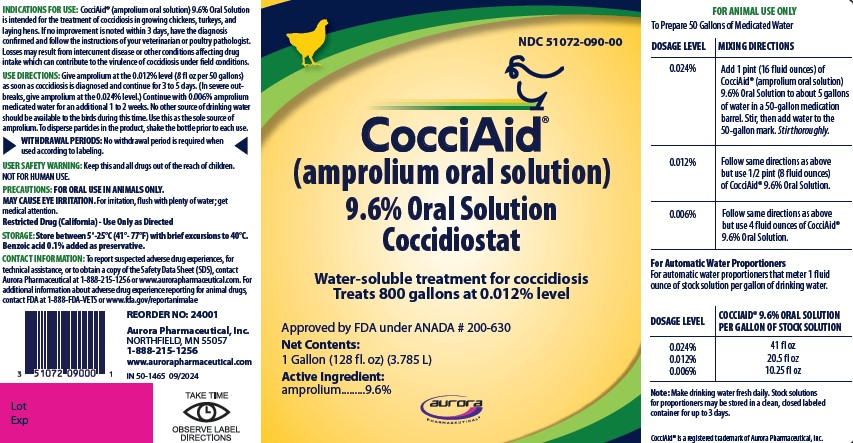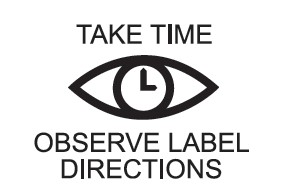 DRUG LABEL: CocciAid
NDC: 51072-090 | Form: SOLUTION
Manufacturer: Aurora Pharmaceutical, Inc.
Category: animal | Type: OTC ANIMAL DRUG LABEL
Date: 20241025

ACTIVE INGREDIENTS: AMPROLIUM 96 1/1 mL
INACTIVE INGREDIENTS: WATER

CocciAid®

(amprolium oral solution)

9.6% Oral Solution

Coccidiostat

Water-soluble treatment for coccidiosis

Treats 800 gallons at 0.012% level

Approved by FDA under ANADA # 200-630

Net Contents:

1 Gallon (128 fl oz) (3.785 L)

Active Ingredient:

amprolium.........9.6%

INDICATIONS FOR USE:

CocciAid® (amprolium oral solution) 9.6% Oral Solution is intended for the treatment of coccidiosis in growing chickens, turkeys, and laying hens. If no improvement is noted within 3 days, have the diagnosis confirmed and follow the instructions of your veterinarian or poultry pathologist. Losses may result from intercurrent disease or other conditions affecting drug intake which can contribute to the virulence of coccidiosis under field conditions.

USE DIRECTIONS:

Give amprolium at the 0.012% level (8 fl oz per 50 gallons) as soon as coccidiosis is diagnosed and continue for 3 to 5 days. (In severe outbreaks, give amprolium at the 0.024% level.) Continue with 0.006% amprolium medicated water for an additional 1 to 2 weeks. No other source of drinking water should be available to the birds during this time. Use as the sole source of amprolium. To disperse particles in the product, shake the bottle prior to each use.

USER SAFETY WARNING:

Keep this and all drugs out of reach of children.
NOT FOR HUMAN USE.

PRECAUTIONS:

FOR ORAL USE IN ANIMALS ONLY.
MAY CAUSE EYE IRRITATION. For irritation, flush with plenty of water; get medical attention.
Restricted Drug (California) — Use Only as Directed

STORAGE:

Store between 5°–25°C (41°–77°F) with brief excursions to 40°C.

Benzoic acid 0.1% added as preservative.

CONTACT INFORMATION:

To report suspected adverse drug experiences, for technical assistance, or to obtain a copy of the Safety Data Sheet (SDS), contact Aurora Pharmaceutical at 1-888-215-1256 or www.aurorapharmaceutical.com. For additional information about adverse drug experience reporting for animal drugs, contact FDA at 1-888-FDA-VETS or www.fda.gov/reportanimalae

REORDER NO: 24001
Aurora Pharmaceutical, Inc.
NORTHFIELD, MN 55057
1-888-215-1256
www.aurorapharmaceutical.com

CocciAid® is a registered trademark of Aurora Pharmaceutical, Inc.

DOSAGE AND ADMINISTRATION

FOR ANIMAL USE ONLY
To Prepare 50 Gallons of Medicated Water

DOSAGE LEVEL | MIXING DIRECTIONS
0.024% | Add 1 pint (16 fluid ounces) of CocciAid® (amprolium oral solution) 9.6% Oral Solution to about 5 gallons of water in a 50-gallon medication barrel. Stir, then add water to the 50-gallon mark. Stir thoroughly.
0.012% | Follow same directions as above but use 1/2 pint (8 fluid ounces) of CocciAid® 9.6% Oral Solution.
0.006% | Follow same directions as above but use 4 fluid ounces of CocciAid® 9.6% Oral Solution.

For Automatic Water Proportioners
For automatic water proportioners that meter 1 fluid ounce of stock solution per gallon of drinking water.

DOSAGE LEVEL | COCCIAID® 9.6% ORAL SOLUTION PER GALLON OF STOCK SOLUTION
0.024% 0.012% 0.006% | 41 fl oz 20.5 fl oz 10.25 fl oz

Note: Make drinking water fresh daily. Stock solutions for proportioners may be stored in a clean, closed labeled container for up to 3 days.

Container Label

PRINCIPAL DISPLAY PANEL - 1 gallon bottle label

IN 50-1465 09/2024